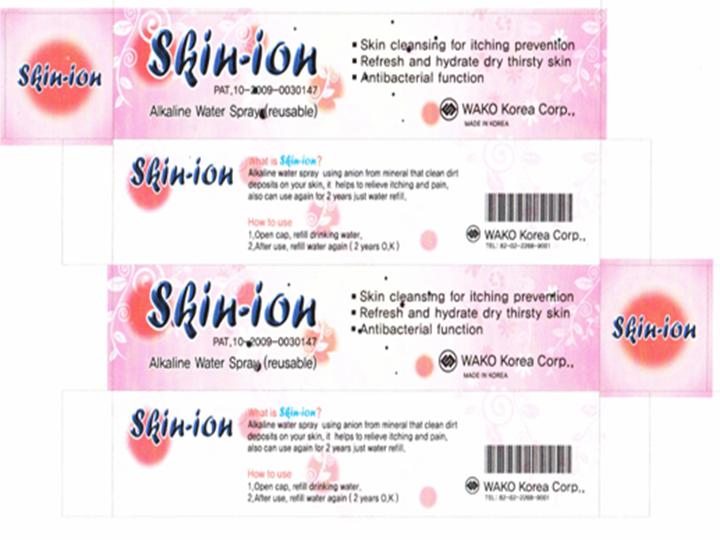 DRUG LABEL: Skin-ion
NDC: 49742-1001 | Form: SPRAY
Manufacturer: WAKO Korea Corp
Category: otc | Type: HUMAN OTC DRUG LABEL
Date: 20091124

ACTIVE INGREDIENTS: ARBUTIN 0.8 mL/40 mL; ADENOSINE 0.016 mL/40 mL; GLYCERIN 0.8 mL/40 mL

ACTIVE INGREDIENT

INGREDIENTS:

WATER, ARBUTIN, GLYCERIN, VITAMIN C, ADENOSINE

WHEN USING

DIRECTION OF USE:

1. Open cap fill water (liquid)

2. After 30 minutes, spray it

3. After use all, refill water (liquid)

DESCRIPTION:

1. Whenever you want to feel freshed:

The Skin-Ion delivers a fine mist of reduced water that refreshes and hydrates dry, thirsty skin. Use several times a day to give yourself a revitalizing lift. In winter, rescue skin from overhead, dry indoor air. Skin-Ion's gentle mist will freshen your look without disturbing your makeup. At the beach or during sports, wash away perspiration and pollutants and restore skin to a natural and healthy pH.

2. Take Skin-Ion when you fly to avoid dry, dehydrated skin. Skin-Ion is even gentle enough for expectant mothers and the delicate skin of young babies. Simply mist the skin of your face, neck, arms and body several fines a day.